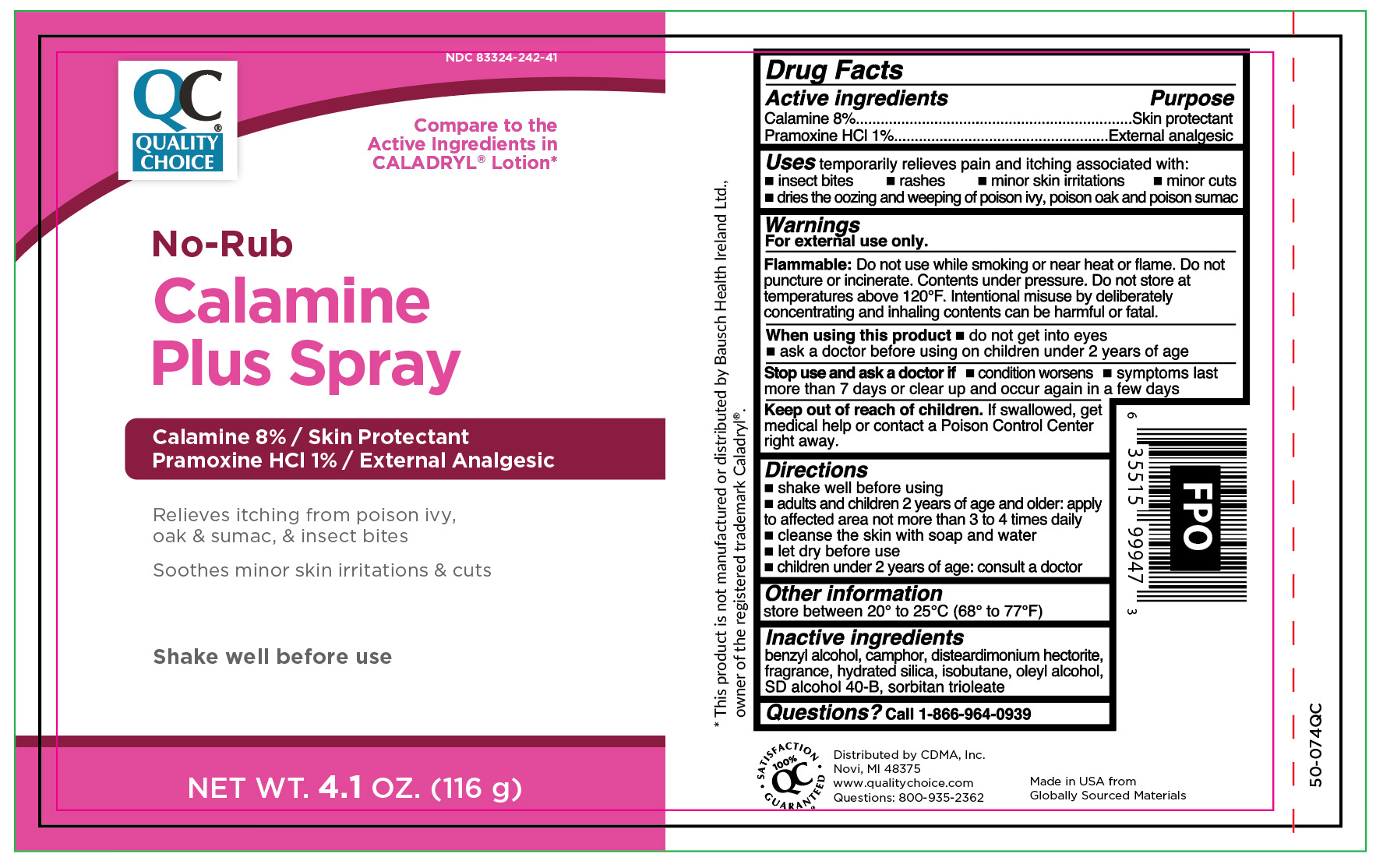 DRUG LABEL: Calamine Plus
NDC: 83324-242 | Form: AEROSOL, SPRAY
Manufacturer: Chain Drug Marketing Association Inc
Category: otc | Type: HUMAN OTC DRUG LABEL
Date: 20251106

ACTIVE INGREDIENTS: FERRIC OXIDE RED 5 mg/1 g; PRAMOXINE HYDROCHLORIDE 10 mg/1 g; ZINC OXIDE 79.5 mg/1 g
INACTIVE INGREDIENTS: CAMPHOR (SYNTHETIC); ISOBUTANE; BENZYL ALCOHOL; OLEYL ALCOHOL; SORBITAN TRIOLEATE; ALCOHOL; HYDRATED SILICA; DISTEARDIMONIUM HECTORITE

Quality Choice Calamine Plus Spray

Active ingredients

Calamine 8%

Pramoxine HCI 1%

Purpose

Skin protectant

External analgesic

Uses

temporarily relieves pain and itching associated with:

- insect bites
- rashes
- minor skin irritations
- minor cuts
- dries the oozing and weeping of poison ivy, poison oak and poison sumac

Warnings

For external use only.

Flammable:

Do not use while smoking or near heat or flame. Do not puncture or incinerate. Contents under pressure. Do not store at temperatures above 120°F. Intentional misuse by deliberately concentrating and inhaling contents can be harmful or fatal.

When using this product

- do not get into eyes
- ask a doctor before using on children under 2 years of age

Stop use and ask a doctor if

- condition worsens
- symptoms last more than 7 days or clear up and occur again in a few days

Keep out of the reach of children.

If swallowed, get medical help or contact a Poison Control Center right away.

Directions

- shake well before using
- adults and children 2 years of age and older: apply to affected area not more than 3 to 4 times daily
- cleanse the skin with soap and water
- let dry before use
- children under 2 years of age: consult a doctor

Other Information

store between 20° to 25°C (68° to 77°F)

Inactive ingredients

benzyl alcohol, camphor, disteardimonium hectorite, fragrance, hydrated silica, isobutane, oleyl alcohol, SD alcohol 40-B, sorbitan trioleate

Questions?

Call 1-866-964-0939

Principal Display Panel

QC

QUALITY CHOICE

No-Rub

NO-RUB

Calamine

Plus Spray

Calamine 8% / Skin Protectant

Pramoxine HCI 1% / External analgesic

Relieves itching from poison ivy,

oak & sumac, & insect bites

Soothes minor skin irritations & cuts

Shake well before use

NET WT 4.1 OZ. (116 g)